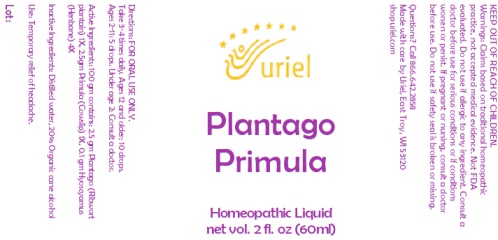 DRUG LABEL: Plantago Primula
NDC: 48951-8400 | Form: LIQUID
Manufacturer: Uriel Pharmacy, Inc.
Category: homeopathic | Type: HUMAN OTC DRUG LABEL
Date: 20231005

ACTIVE INGREDIENTS: PLANTAGO MAJOR LEAF 1 [hp_X]/1 mL; PRIMULA VERIS FLOWER 1 [hp_X]/1 mL; HYOSCYAMUS NIGER LEAF 4 [hp_X]/1 mL
INACTIVE INGREDIENTS: WATER; ALCOHOL

Plantago Primula

INDICATIONS AND USAGE

Directions: FOR ORAL USE ONLY.

DOSAGE AND ADMINISTRATION

Take 3-4 times daily. Ages 12 and older: 10 drops. Ages 2-11: 5 drops. Under age 2: Consult a doctor.

ACTIVE INGREDIENT

Active Ingredients: 100 gm contains: 2.5 gm Plantago (Ribwort plantain) 1X, 2.5gm Primula (Cowslip) 1X, 0.1 gm Hyoscyamus (Henbane) 4X

Inactive Ingredients: Distilled water, 20% Organic cane alcohol

PURPOSE

Use: Temporary relief of headache.

KEEP OUT OF REACH OF CHILDREN.

WARNINGS

Warnings: Claims based on traditional homeopathic practice, not accepted medical evidence. Not FDA evaluated.
Do not use if allergic to any ingredient. Consult a doctor before use for serious conditions or if conditions worsen or persist. If pregnant or nursing, consult a doctor before use. Do not use if safety seal is broken or missing.

Questions? Call 866.642.2858
Made with care by Uriel, East Troy, WI 53120
shopuriel.com Lot: